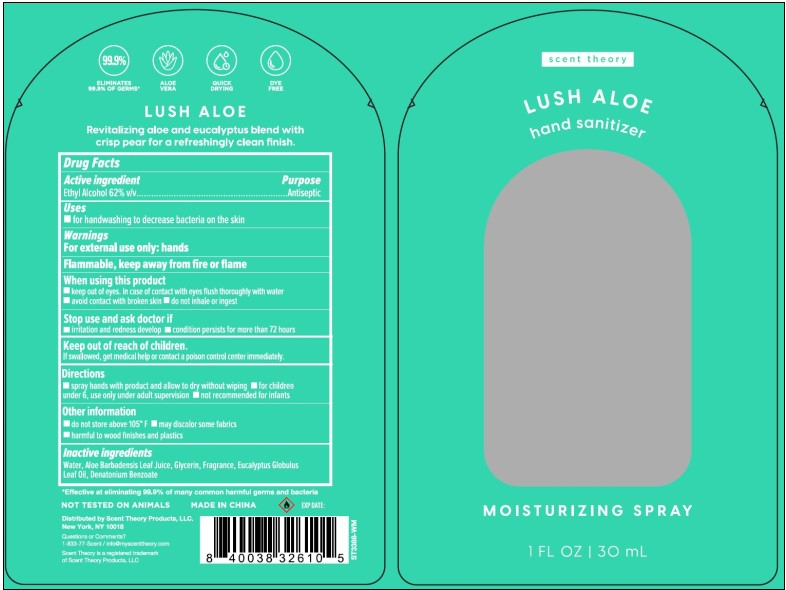 DRUG LABEL: HAND SANITIZER
NDC: 76891-139 | Form: SPRAY
Manufacturer: SCENT THEORY PRODUCTS LLC
Category: otc | Type: HUMAN OTC DRUG LABEL
Date: 20241017

ACTIVE INGREDIENTS: ALCOHOL 62 mL/100 mL
INACTIVE INGREDIENTS: WATER; GLYCERIN; ALOE VERA LEAF; DENATONIUM BENZOATE; EUCALYPTUS GLOBULUS LEAF

SCENT THEORY - HAND SANITIZER - MOISTURIZING SPRAY - 62% ALCOHOL - LUSH ALOE (76891-139)

ACTIVE INGREDIENT

ETHYL ALCOHOL 62% V/V

PURPOSE

ANTISEPTIC

USES

FOR HANDWASHING TO DECREASE BACTERIA ON THE SKIN.

WARNINGS

FOR EXTERNAL USE ONLY: HANDS

FLAMMABLE, KEEP AWAY FROM FIRE OR FLAME.

WHEN USING THIS PRODUCT

- KEEP OUT OF EYES. IN CASE OF CONTACT WITH EYES, FLUSH THOROUGHLY WITH WATER.
- AVOID CONTACT WITH BROKEN SKIN.
- DO NOT INHALE OR INGEST.

STOP USE AND ASK A DOCTOR IF

- IRRITATION AND REDNESS DEVELOP
- CONDITION PERSISTS FOR MORE THAN 72 HOURS

Keep out of reach of children.

If swallowed, get medical help or contact a Poison Control Center right away.

DIRECTIONS

- SPRAY HANDS WITH PRODUCT AND ALLOW TO DRY WITHOUT WIPING
- FOR CHILDREN UNDER 6, USE ONLY UNDER ADULT SUPERVISION
- NOT RECOMMENDED FOR INFANTS

OTHER INFORMATION

- DO NOT STORE ABOVE 105°F
- MAY DISCOLOR SOME FABRICS
- HARMFUL TO WOOD FINISHES AND PLASTICS

INACTIVE INGREDIENTS

WATER, ALOE BARBADENSIS LEAF JUICE, GLYCERIN, FRAGRANCE, EUCALYPTUS GLOBULUS LEAF OIL, DENATONIUM BENZOATE